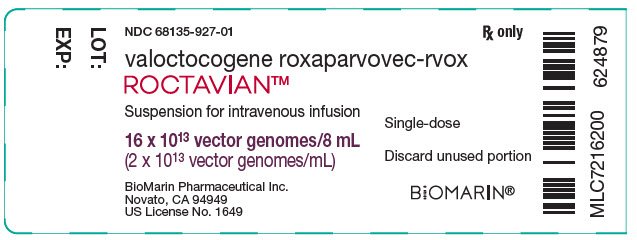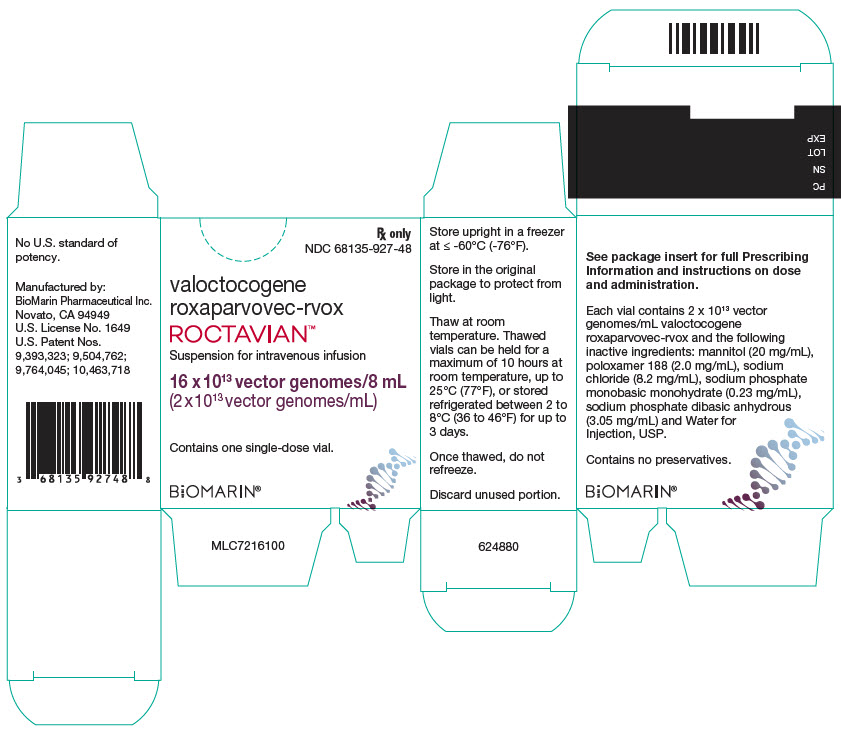 DRUG LABEL: ROCTAVIAN
NDC: 68135-927 | Form: INJECTION, SUSPENSION
Manufacturer: BioMarin Pharmaceutical Inc.
Category: prescription | Type: HUMAN PRESCRIPTION DRUG LABEL
Date: 20230629

ACTIVE INGREDIENTS: VALOCTOCOGENE ROXAPARVOVEC 20000000000000 {GC}/1 mL

HIGHLIGHTS OF PRESCRIBING INFORMATION

These highlights do not include all the information needed to use ROCTAVIAN safely and effectively. See full prescribing information for ROCTAVIAN.
ROCTAVIAN (valoctocogene roxaparvovec-rvox) suspension for intravenous infusion
Initial U.S. Approval: 2023

1 INDICATIONS AND USAGE

ROCTAVIAN is an adeno-associated virus vector-based gene therapy indicated for the treatment of adults with severe hemophilia A (congenital factor VIII deficiency with factor VIII activity < 1 IU/dL) without pre-existing antibodies to adeno-associated virus serotype 5 detected by an FDA-approved test. (1)

2 DOSAGE AND ADMINISTRATION

For one-time single-dose intravenous use only. (2)

- Perform baseline testing to select patients, including testing for pre-existing antibodies to adeno-associated virus serotype 5 (AAV5), factor VIII inhibitor presence, and liver health assessments. (2)
- The recommended dose of ROCTAVIAN is 6 × 10^13 vector genomes (vg) per kg of body weight. (2.1)
- Start the infusion at 1 mL/min. If tolerated, the rate may be increased every 30 minutes by 1 mL/min up to a maximum rate of 4 mL/min. (2.1)

3 DOSAGE FORMS AND STRENGTHS

- ROCTAVIAN is a suspension for intravenous infusion. (3)
- ROCTAVIAN has a nominal concentration of 2 × 10^13 vg valoctocogene roxaparvovec-rvox per mL, each vial contains an extractable volume of not less than 8 mL (16 × 10^13 vg). (3)

4 CONTRAINDICATIONS

- Active infections, either acute or uncontrolled chronic. (4)
- Known significant hepatic fibrosis (stage 3 or 4), or cirrhosis. (4)
- Known hypersensitivity to mannitol. (4)

5 WARNINGS AND PRECAUTIONS

- Infusion-related reactions: Infusion reactions, including hypersensitivity reactions and anaphylaxis, have occurred. Monitor during and for at least 3 hours after ROCTAVIAN administration. If symptoms occur, slow or interrupt administration and give appropriate treatment. Restart infusion at slower rate once symptoms resolve. Discontinue infusion for anaphylaxis. (2.3, 5.1)
- Hepatotoxicity: Monitor alanine aminotransferase (ALT) weekly for at least 26 weeks and institute corticosteroid treatment in response to ALT elevations as required. Continue to monitor ALT until it returns to baseline. Monitor factor VIII activity levels since ALT elevation may be accompanied by a decrease in factor VIII activity. Monitor for and manage adverse reactions from corticosteroid use. (5.2)
- Thromboembolic events: Thromboembolic events may occur in the setting of elevated factor VIII activity above the upper limit of normal (ULN). Factor VIII activity above ULN has been reported following ROCTAVIAN infusion. Evaluate for risk factors for thrombosis including cardiovascular risk factors prior to and after ROCTAVIAN use and advise patients accordingly. (5.3)
- Monitoring laboratory tests: Monitor for factor VIII activity and factor VIII inhibitors. (5.4)
- Malignancy: Monitor for hepatocellular malignancy in patients with risk factors for hepatocellular carcinoma (e.g., hepatitis B or C, non-alcoholic fatty liver disease, chronic alcohol consumption, non-alcoholic steatohepatitis, advanced age). Perform regular liver ultrasound (e.g., annually) and alpha-fetoprotein testing following administration. In the event that any malignancy occurs after treatment with ROCTAVIAN, contact BioMarin Pharmaceutical Inc. at 1-866-906-6100. (5.5)

6 ADVERSE REACTIONS

- Most common adverse reactions (incidence ≥ 5%) were nausea, fatigue, headache, infusion-related reactions, vomiting, and abdominal pain. (6)
- Most common laboratory abnormalities (incidence ≥ 10%) were ALT, aspartate aminotransferase (AST), lactate dehydrogenase (LDH), creatine phosphokinase (CPK), factor VIII activity levels, gamma-glutamyl transferase (GGT) and bilirubin > ULN. (6)

To report SUSPECTED ADVERSE REACTIONS, contact BioMarin Pharmaceutical Inc. at 1-866-906-6100, or FDA at 1-800-FDA-1088 or www.fda.gov/medwatch.

8 USE IN SPECIFIC POPULATIONS

- For 6 months after administration, men must not donate semen, and men and their female partners must prevent or postpone pregnancy. (8.3)
- There is limited information on the safety and effectiveness of ROCTAVIAN in patients with HIV infection. (8.6)
- The safety and effectiveness of ROCTAVIAN in patients with prior or active factor VIII inhibitors have not been established. (8.7)

FULL PRESCRIBING INFORMATION

1 INDICATIONS AND USAGE

ROCTAVIAN is an adeno-associated virus vector-based gene therapy indicated for the treatment of adults with severe hemophilia A (congenital factor VIII deficiency with factor VIII activity < 1 IU/dL) without antibodies to adeno-associated virus serotype 5 (AAV5) detected by an FDA-approved test.

2 DOSAGE AND ADMINISTRATION

For one-time single-dose intravenous use only.

Treatment with ROCTAVIAN should be under the supervision of a physician experienced in the treatment of hemophilia and/or bleeding disorders.

For Patient Selection

- Perform testing for pre-existing antibodies to AAV5 using the FDA approved companion diagnostic.
  DO NOT administer ROCTAVIAN to patients with a positive test for antibodies to AAV5. Information on FDA-approved tests for the detection of antibodies to AAV5 is available at: http://www.fda.gov/CompanionDiagnostics.
- Perform factor VIII inhibitor titer testing [see Use in Specific Populations (8.7) and Clinical Pharmacology (12.6)].
  DO NOT administer ROCTAVIAN to a patient with a positive test for factor VIII inhibitor.
- Perform liver health assessments, which include:
  - Liver function tests [alanine aminotransferase (ALT), aspartate aminotransferase (AST), gamma-glutamyl transferase (GGT), alkaline phosphatase (ALP), total bilirubin and international normalized ration (INR)]
  - Ultrasound and elastography or laboratory assessments for liver fibrosis
  In case of radiological liver abnormalities and/or liver function test abnormalities (ALT, AST, GGT, ALP or total bilirubin > 1.25 × ULN or INR ≥ 1.4), consider a consultation with a hepatologist to assess eligibility for ROCTAVIAN.
- Assess patient's ability to receive corticosteroids and/or other immunosuppressive therapy that may be required for an extended period [see Dosage and Administration (2.3)]. Ensure that the risks associated with immunosuppression are acceptable for the individual patient.
- DO NOT administer ROCTAVIAN to patients with active acute or uncontrolled chronic infections, known significant hepatic fibrosis (stage 3 or 4 on the Batts-Ludwig scale or equivalent) or cirrhosis, or mannitol hypersensitivity [see Contraindications (4) and Use in Specific Populations (8.8)].

2.1 Dose

The recommended dose of ROCTAVIAN is 6 × 10^13 vector genomes per kilogram (vg/kg) body weight, administered as a single intravenous infusion. ROCTAVIAN is administered using an infusion pump at a rate of 1 mL/min, which can be increased every 30 minutes by 1 mL/min up to a maximum rate of 4 mL/min.

Calculating Dose in Milliliters (mL) and Number of Vials Required

- Patient dose volume in mL:
  Body weight in kg multiplied by 3 = dose in mL.
  The multiplication factor 3 represents the per kilogram dose (6 × 10^13 vg/kg) divided by the amount of vector genomes per mL of the ROCTAVIAN suspension (2 × 10^13 vg/mL).
- Number of ROCTAVIAN vials to be thawed:
  Patient dose volume (mL) divided by 8 = number of vials to be thawed (round up to next whole number of vials).
  The division factor 8 represents the minimum volume of ROCTAVIAN extractable from a vial (8 mL).

Table 1: Example of Dose Volume and Number of Vials to be Thawed
Patient Weight | Patient Dose by Volume (mL) (body weight multiplied by 3) | Number of Vials to be Thawed (dose volume divided by 8, then rounded up)
70 kg | 210 mL | 27 vials (rounded up from 26.25)

ROCTAVIAN can be administered only once.

2.2 Preparation for Administration

Required Equipment and Materials

- Flow rate-controlled syringe pump
- Syringes for ROCTAVIAN administration (the number of syringes will depend on the patient's dose volume and the syringe pump used and should be prepared prior to administration of ROCTAVIAN)
- 18- to 21-gauge sharp needles
- High-volume, in-line, low protein binding infusion filter with a pore size of 0.22 microns and maximum operating pressure adequate for the syringe pump or pump settings. Ensure availability of a sufficient number of replacement filters, according to the specifications for maximum filtered fluid volume.
- Syringe of 0.9% Sodium Chloride Injection, USP sodium chloride 9 mg/mL (0.9%) solution for priming and flushing the infusion line
- When assembling the infusion system, refer to the compatible materials with ROCTAVIAN suspension listed in Table 2.

Table 2: Compatible Infusion System Component Materials
Component | Compatible Materials
Syringes | Polypropylene barrel with a synthetic rubber plunger tip
Syringe cap | Polypropylene
Infusion tubing [Tubing extensions should not exceed 40 inches in length.] | Polyethylene
0.22 micron in-line filter | Polyvinylidene fluoride filter with polyvinyl chloride body
Infusion catheter | Polyurethane based polymer
Stopcocks | Polycarbonate
18 to 21-gauge sharp needles for extraction from vials [Do not use filter needles to extract ROCTAVIAN from vials.] | Stainless steel

General Precautions

- Do not expose ROCTAVIAN to the light of an ultraviolet radiation disinfection lamp.
- Prepare ROCTAVIAN using aseptic technique. Wear gloves and safety glasses during preparation and administration.
- Treat spills of ROCTAVIAN with a virucidal agent with proven activity against non-enveloped viruses and blot using absorbent materials.
- Dispose unused medicinal product and materials that may have come in contact with ROCTAVIAN in accordance with the local biosafety guidelines.

Thaw and Inspect

1. Keep each vial in its carton until ready to thaw. ROCTAVIAN is sensitive to light.
2. Thaw ROCTAVIAN at room temperature. Do not thaw or warm vials any other way. Thawing time is approximately 2 hours.
3. Remove the required number of vials from their cartons.
4. Inspect the vials for damage to the vial or cap. Do not use if damaged.
5. Set the vials upright. To achieve optimal thawing, spread them out evenly or place them in racks that have been kept at room temperature.
6. Visually confirm that all vials have been thawed. There should be no visible ice.
7. Very gently invert each vial 5 times to mix. It is important to minimize foaming.
8. Let the suspension settle for approximately 5 minutes before continuing.
9. Visually inspect the fully thawed vials. Do not use a vial if the suspension is not clear, not colorless to pale yellow, or contains visible particles.

ROCTAVIAN contains no preservative. For microbiological safety, keep the thawed suspension in the vials until it is time for infusion.

If necessary, an intact vial (stopper not yet punctured) that has been thawed at room temperature can be stored refrigerated between 2 to 8°C (36 to 46°F) for up to 3 days, upright and protected from light (e.g., in the original carton).

Thawed ROCTAVIAN (in vials or syringes) can be held at room temperature, up to 25°C (77°F), for a maximum of 10 hours including hold time in intact vial, preparation time into the syringes, and duration of infusion.

Extraction into Syringes

10. Using 18 to 21-gauge sharp needles, slowly extract ROCTAVIAN from the vials into the infusion-pump syringes. All infusion-pump syringes should be prepared prior to administering ROCTAVIAN. The contents of multiple vials may be combined into a single syringe.

Addition of In-line Filter and Priming of the Infusion System

11. Insert the in-line filter close to the infusion site.
12. Prime tubing and filter with ROCTAVIAN.
13. When replacing filters during the infusion, use 0.9% Sodium Chloride Injection, USP, for priming and flushing.

Incompatibilities

Do not use infusion system components other than those described in Table 2. ROCTAVIAN must not be mixed or diluted with infusion solutions; 0.9% Sodium Chloride Injection, USP is used to prime and flush the infusion line.

2.3 Administration

- Administer ROCTAVIAN in a setting where personnel and equipment are immediately available to treat infusion-related reactions [see Warnings and Precautions (5.1)].
- Infuse the suspension through a suitable peripheral vein, using an infusion catheter with in-line filter and a programmable syringe pump.
- Start the infusion at a rate of 1 mL/min. If tolerated, the rate may be increased every 30 minutes by 1 mL/min up to a maximum rate of 4 mL/min. The infusion time depends on infusion volume, rate and patient response and can be, for example, 2 to 5 hours or longer for a patient weighing 100 kg.
- In the event of an infusion-related reaction during administration [see Warnings and Precautions (5.1)],
  - Decrease the infusion rate or stop the infusion.
  - Administer treatment as needed to manage infusion reaction.
  - If the infusion is stopped, restart the infusion at a rate of 1 mL/min and consider maintaining it at a previously tolerated level for the remainder of the infusion. If the infusion needs to be restarted, the infusion should be completed within 10 hours of initial drug product thaw.
  - Discontinue infusion for anaphylaxis.
- DO NOT administer ROCTAVIAN as an intravenous push or bolus.
- DO NOT infuse ROCTAVIAN in the same intravenous line with any other products.
- DO NOT use a central line or port.
- To ensure the patient receives the complete dose, after the content of the last ROCTAVIAN-containing syringe is infused, flush the infusion line with a sufficient volume of 0.9% Sodium Chloride Injection, USP, through the same tubing and filter, and at the same infusion rate.
- Maintain venous access during the subsequent observation period [see Warnings and Precautions (5.1)].

Monitoring Post-Administration

Conduct the following tests after ROCTAVIAN administration [see Warnings and Precautions (5.2, 5.4, 5.5)].

- Perform regular ALT testing to monitor for elevations. Elevated liver enzymes, especially elevated ALT, may indicate immune-mediated hepatotoxicity and may be associated with decline in factor VIII activity.
  The monitoring schedule for ALT, and recommendations for corticosteroid use (initiation and taper) are based on the clinical efficacy and safety experience of 112 patients in a clinical study with ROCTAVIAN.
  - Monitor ALT weekly for at least 26 weeks following administration of ROCTAVIAN. See Table 3 for monitoring schedule. Monitor AST and creatine phosphokinase (CPK) as needed to help rule out alternative causes for ALT elevations (including potentially hepatotoxic medications or agents, alcohol consumption, or strenuous exercise). Consider repeating ALT testing within 24 to 48 hours to confirm ALT elevation prior to initiation of corticosteroid treatment and using the same laboratory to measure ALT activity at baseline and over time to minimize the impact of inter-laboratory variability on test results.
  - If ALT ≥ 1.5 × baseline or above ULN consider corticosteroid treatment. For patients who need corticosteroid therapy, the recommended starting dose is 60 mg with a subsequent taper upon return of ALT levels to baseline (see Table 4 below for recommendation on corticosteroid treatment).
  - Monitor ALT weekly, and as clinically indicated, during corticosteroid therapy. Continue to monitor ALT until its return to baseline.
  - Monitor for and manage adverse reactions secondary to corticosteroid use. Refer to the corticosteroid prescribing information for risks and required precautions.

Table 3: ALT Monitoring Post-Administration [Monitoring of ALT may be accompanied by monitoring of AST and CPK to rule out other causes of ALT elevation.]
Timeframe | Monitoring Frequency [Weekly monitoring is recommended, and as clinically indicated, during corticosteroid tapering.]
First 26 weeks | Weekly
Weeks 26 to 52 (Year 1) | Every 1 to 2 weeks
Year 2 | Every 3 months
After Year 2 | Every 6 months

Table 4: Recommended Corticosteroid Regimen in Response to ALT Elevations
 | Corticosteroid Regimen (Prednisone or Equivalent Dose of Another Corticosteroid)
Starting Dose [If ALT continues to rise or has not improved after 2 weeks, increase the corticosteroid dose up to a maximum of 1.2 mg/kg, after ruling out alternative causes for ALT elevation.] | 60 mg daily for 2 weeks
Tapering [Taper corticosteroids after ALT levels reach baseline. The taper may be individualized based on the trend of ALT decline, the patient's medical condition, corticosteroid tolerance, and adverse reactions to corticosteroid therapy.] | 40 mg daily for 3 weeks 30 mg daily for 1 week 20 mg daily for 1 week 10 mg daily for 1 week

There is limited information on the benefit of starting a corticosteroid course after the first year of ROCTAVIAN administration.

Other immunosuppressive therapies (e.g., tacrolimus, mycophenolate mofetil) may be considered if corticosteroids are contraindicated, ineffective or there are adverse reactions secondary to corticosteroid use necessitating discontinuation.

- Monitor Factor VIII Activity
  - Monitor factor VIII activity using the same schedule for ALT monitoring in Table 3 [see Warnings and Precautions (5.4)].
  - Consider more frequent monitoring in patients with factor VIII activity levels ≤ 5 IU/dL and evidence of bleeding, taking into account the stability of factor VIII levels since the previous measurement.
  - It may take several weeks after ROCTAVIAN infusion before ROCTAVIAN-derived factor VIII activity rises to a level sufficient for prevention of spontaneous bleeding episodes. Therefore, continued routine prophylaxis support with exogenous factor VIII or other hemostatic products used in the management of hemophilia A may be needed during the first few weeks after ROCTAVIAN infusion [see Clinical Pharmacology (12.3)]. Exogenous factor VIII or other hemostatic products may also be required in case of surgery, invasive procedures, trauma, or bleeds in the event that ROCTAVIAN-derived factor VIII activity is deemed insufficient for adequate hemostasis in such situations.
  - The use of different assays may impact test results; therefore, use the same assay and reagents to monitor patients over time, if feasible [see Warnings and Precautions (5.4)].
  - Use of exogenous factor VIII products before and after ROCTAVIAN administration may impede assessment of ROCTAVIAN-derived factor VIII activity.
- Monitor patients for factor VIII inhibitors (neutralizing antibodies to factor VIII). Test for factor VIII inhibitors especially if bleeding is not controlled, or plasma factor VIII activity levels decrease [see Warnings and Precautions (5.4) and Clinical Pharmacology (12.6)].
- Perform regular liver ultrasound (e.g., annually) and alpha-fetoprotein (AFP) testing in patients with risk factors of hepatocellular carcinoma (e.g., hepatitis B or C, non-alcoholic fatty liver disease, chronic alcohol consumption, non-alcoholic steatohepatitis, advanced age) [see Warnings and Precautions (5.5)].

3 DOSAGE FORMS AND STRENGTHS

ROCTAVIAN is a clear, colorless to pale yellow suspension for intravenous infusion containing 2 × 10^13 vg valoctocogene roxaparvovec-rvox per mL.

ROCTAVIAN is provided in vials containing an extractable volume of not less than 8 mL.

Dose volume is based on body weight, with a recommended dose of 6 × 10^13 vg/kg.

4 CONTRAINDICATIONS

Administration of ROCTAVIAN is contraindicated in:

- patients with active infections, either acute (such as acute respiratory infections or acute hepatitis) or uncontrolled chronic (such as chronic active hepatitis B).
- patients with known significant hepatic fibrosis (stage 3 or 4 on the Batts-Ludwig scale or equivalent), or cirrhosis [see Dosage and Administration (2)].
- patients with known hypersensitivity to mannitol.

5 WARNINGS AND PRECAUTIONS

5.1 Infusion-Related Reactions

Infusion-related reactions, including hypersensitivity reactions and anaphylaxis, have occurred during and/or following ROCTAVIAN administration. Symptoms included one or more of the following: urticaria, pruritus, rash, sneezing, coughing, dyspnea, rhinorrhea, watery eyes, tingling throat, nausea, diarrhea, hypotension, tachycardia, presyncope, pyrexia, rigors, and chills.

Monitor patients during and for at least 3 hours after completion of ROCTAVIAN infusion. Do not infuse the product faster than 4 mL/min [see Dosage and Administration (2.3)].

In the event of an infusion reaction, administration of ROCTAVIAN should be slowed or stopped. Restart at a lower rate after the infusion reaction has resolved. Discontinue infusion for anaphylaxis. Consider treatment with a corticosteroid, antihistamine, and other measures for management of an infusion reaction [see Dosage and Administration (2.3)].

5.2 Hepatotoxicity

Intravenous administration of a liver-directed AAV vector could lead to liver enzyme elevations (transaminitis), especially ALT elevation. Transaminitis is presumed to occur due to immune-mediated injury of transduced hepatocytes and may reduce the therapeutic efficacy of AAV-vector based gene therapy.

Majority of patients treated with ROCTAVIAN experienced ALT elevations. Most ALT elevations occurred within the first year following ROCTAVIAN administration, especially within the first 26 weeks, were low-grade, and resolved. The median time (range) to the first ALT elevation (defined as ALT ≥ 1.5 × baseline or above ULN) was 7 weeks (0.4, 159 weeks) and the median duration (range) was 4 weeks (0.1, 135 weeks). Some ALT elevations were associated with a decline in factor VIII activity.

The majority of the 112 patients in the clinical trial of ROCTAVIAN required corticosteroids for ALT elevation [see Adverse Reactions (6.1) and Clinical Studies (14)]. The median duration (range) of corticosteroid use was 35 weeks (3, 120 weeks). The median duration (range) of alternate immunosuppressive medications use was 26 weeks (6, 118 weeks). In 20 (18%) patients the duration of immunosuppression was > 1 year.

Monitor ALT and institute corticosteroid treatment in response to ALT elevations, as required. Monitor ALT and factor VIII activity levels weekly and, as clinically indicated, during corticosteroid therapy [see Dosage and Administration (2.3)]. Monitor for and manage adverse reactions secondary to corticosteroid therapy.

Since some ALT elevations have been attributed to alcohol consumption in clinical studies, patients should abstain from alcohol consumption for at least a year following ROCTAVIAN infusion and limit alcohol use thereafter. Concomitant medications may cause hepatotoxicity, or decrease factor VIII activity, or change plasma corticosteroid levels which may impact liver enzyme elevation and/or factor VIII activity [see Drug Interactions (7.0, 7.1, 7.2)]. Closely monitor concomitant medication use including herbal products and nutritional supplements and consider alternative medications in case of potential drug interactions.

5.3 Thromboembolic Events

Elevated factor VIII activity level above the ULN as measured by the chromogenic substrate assays (CSA), or one-stage clotting assays (OSA), or both assays has occurred following ROCTAVIAN administration. Thirty-eight (28%) patients experienced elevations of factor VIII above ULN with a median time to first occurrence of 14 weeks and a median total duration above ULN of 12 weeks.

An increase in factor VIII activity may increase the risk for venous and arterial thromboembolic events. There are no data in patients with a history of venous or arterial thromboembolism or known history of thrombophilia since such patients were excluded from clinical trials of ROCTAVIAN.

Evaluate patients for risk of thrombosis including general cardiovascular risk factors before and after administration of ROCTAVIAN. Advise patients on their individual risk of thrombosis in relation to their factor VIII activity levels above ULN and consider prophylactic anticoagulation. Advise patients to seek immediate medical attention for signs or symptoms indicative of a thrombotic event.

5.4 Monitoring Laboratory Tests

Factor VIII Assays

Factor VIII activity produced by ROCTAVIAN in human plasma is higher if measured with OSA compared to CSA. In clinical studies, there was a high correlation between OSA and CSA factor VIII activity levels across the entire range of each assay's results [doi: 10.1182/blood.2020005683]. For routine clinical monitoring of factor VIII activity levels, either assay may be used. The conversion factor between the assays can be approximated based on clinical study results (central laboratory) to be: OSA = 1.5 × CSA. For example, a factor VIII activity level of 50 IU/dL using CSA calculates to a level of 75 IU/dL using OSA. The OSA to CSA ratio depends on the factor VIII assay reagents used by the laboratory and can range from 1.3 to 2.0, therefore, the same type of OSA or CSA reagents should be used to monitor factor VIII levels over time.

When switching from hemostatic products prior to ROCTAVIAN treatment, physicians should refer to the relevant prescribing information to avoid the potential for factor VIII activity assay interference during the transition period.

Factor VIII Inhibitors

Monitor patients through appropriate clinical observations and laboratory tests for the development of factor VIII inhibitors after ROCTAVIAN administration. Perform an assay that detects factor VIII inhibitors if bleeding is not controlled, or plasma factor VIII activity levels decrease [see Dosage and Administration (2.3)].

5.5 Malignancy

The integration of liver-targeting AAV vector DNA into the genome may carry the theoretical risk of hepatocellular carcinoma development.

ROCTAVIAN is composed of a non-replicating AAV5 vector whose DNA persists largely in episomal form. Low levels of vector integration were found following evaluation of liver samples from 5 patients and parotid gland tissue sample from 1 patient in clinical studies and liver samples from 12 nonhuman primates [see Clinical Pharmacology (12.2) and Nonclinical Toxicology (13.1)]. ROCTAVIAN can also insert into the DNA of other human body cells. No malignancies assessed as being likely related to ROCTAVIAN were observed in clinical studies.

Monitor patients with risk factors for hepatocellular carcinoma (e.g., hepatitis B or C, non-alcoholic fatty liver disease, chronic alcohol consumption, non-alcoholic steatohepatitis, advanced age) with regular liver ultrasound (e.g., annually) and alpha-fetoprotein testing for 5 years following ROCTAVIAN administration [see Dosage and Administration (2.3)].

In the event that a malignancy occurs, contact BioMarin Pharmaceutical Inc. at 1-866-906-6100 to obtain instructions on collecting patient samples for testing.

6 ADVERSE REACTIONS

The following adverse reactions are also discussed in other sections of the label:

- Infusion-Related Reactions [see Warnings and Precautions (5.1)]
- Hepatotoxicity [see Warnings and Precautions (5.2)]

6.1 Clinical Trials Experience

Because clinical trials are conducted under widely varying conditions, adverse reaction rates observed in the clinical trials of a drug cannot be directly compared to rates in the clinical trials of another drug and may not reflect the rates observed in practice.

The safety data described in this section reflect the exposure of 134 adult patients with severe hemophilia A (defined as residual factor VIII activity ≤ 1 IU/dL) to a single dose of 6 × 10^13 vg/kg of body weight of ROCTAVIAN. Patients with detectable pre-existing antibodies to AAV5, active infections, history of thrombosis, immunosuppressive disorders, and liver dysfunction were excluded. All patients had a median follow-up of 162 weeks (range: 66 to 255 weeks) [see Clinical Studies (14)].

The most common adverse reactions (≥ 5%) to ROCTAVIAN were nausea, fatigue, headache, infusion-related reactions, vomiting, and abdominal pain.

The most common laboratory abnormalities (≥ 10%) to ROCTAVIAN were ALT, AST, LDH, CPK, factor VIII activity levels, GGT, and bilirubin > ULN.

Non-laboratory adverse reactions (≥ 5%) to ROCTAVIAN are listed in Table 5. There were 6 serious adverse reactions related to ROCTAVIAN treatment including ALT elevation, presyncope, maculopapular rash, anaphylaxis, and hypersensitivity reaction.

Table 5: Adverse Reactions in ≥ 5% [Other adverse reactions include gastroenteritis (2 patients; 1%), rash (2 patients; 1%), diarrhea (6 patients; 4%), and dizziness (3 patients; 2%).] of Patients Treated with ROCTAVIAN
Adverse Reactions | Number of Patients (%) N = 134
Adverse Reactions | All Grades | ≥ Grade 3
Nervous system disorders
Headache | 9 (7%) | 0 (0%)
Gastrointestinal disorders
Nausea | 42 (31%) | 0 (0%)
Vomiting | 8 (6%) | 0 (0%)
Abdominal pain [Includes abdominal discomfort, abdominal distension, abdominal tenderness, and abdominal pain upper.] | 8 (6%) | 0 (0%)
General disorders and administration site conditions
Fatigue [Includes fatigue, lethargy, and malaise.] | 21 (16%) | 0 (0%)
Infusion-related reactions [Infusion-related reactions are not under a specific system organ class and include multiple symptoms that occurred during or within 6 hours after the end of infusion [see Warnings and Precautions (5.1)].] | 9 (7%) | 2 (1%)

Table 6 lists laboratory abnormalities in patients treated with ROCTAVIAN.

Table 6: Laboratory Abnormalities in Patients Treated with ROCTAVIAN
Laboratory Abnormalities | Number of Patients (%) N = 134
ALT increases > ULN | 109 (81%)
AST increases > ULN | 92 (69%)
LDH increases > ULN | 77 (57%)
CPK increases > ULN | 60 (45%)
Factor VIII activity levels > ULN [Patients with one or more instances of factor VIII activity levels > 170 IU/dL (ULN of the CSA used) or > 150 IU/dL (ULN of the OSA used) [see Warnings and Precautions (5.3)].] | 38 (28%)
GGT increases > ULN | 24 (18%)
Bilirubin increases > ULN | 18 (13%)

Twelve (9%), 9 (7%) and 1 (1%) of patients experienced > 5-20 × ULN ALT, AST and GGT elevations, respectively. Seven (5%) patients and 5 (4%) patients experienced > 5-10 × ULN and > 10 × ULN CPK increases, respectively.

Infusion-related reactions were observed in 9 patients (7%), including hypersensitivity reactions (4%) and anaphylaxis (1%), and have occurred during and/or following ROCTAVIAN administration.

Hepatotoxicity as defined by ALT ≥ 1.5 × baseline or ALT > ULN occurred in 107 of 112 (96%) patients. Nine (8%) patients had ALT between > 5-20 × ULN. One hundred (89%) patients had ALT elevations that occurred within the first 26 weeks, 74 (66%) patients had ALT elevations that occurred between weeks 27 to 52, and 72 (64%) patients had ALT elevations that occurred beyond 52 weeks after administration. Thirty-four of 112 (30%) patients had ALT elevations that were associated with a decline in factor VIII activity of ≥ 30%.

The majority of patients (82%, 92/112) required corticosteroids for one or more episodes of ALT elevation while 35% (39/112) required alternate immunosuppression. Seventy-six percent, 5%, and 1% of patients used corticosteroids within the first 26 weeks, weeks 27 to 52, and beyond 52 weeks respectively following ROCTAVIAN administration.

The most common (≥ 10%) adverse reactions from corticosteroid use (N = 92) included acne (34%), insomnia (27%), mood disorders (20%), cushingoid (20%), rash (18%), weight gain (16%), hypertension (12%), folliculitis (11%), abdominal pain (10%), and vision disorders (10%). Other clinically meaningful adverse events while on corticosteroid therapy included bone fracture (5%), impaired glucose tolerance (5%), herpes zoster (3%), oral candidiasis (3%), and adrenal insufficiency (1%). The most common adverse reactions from alternate immunosuppressant use (N = 39) included hypomagnesemia (15%) and diarrhea (10%). Infections requiring intravenous antimicrobial therapy occurred in 3 (3%) patients while on corticosteroid or other immunosuppressant therapy (N = 97).

One case of autoimmune hepatitis was reported during third year follow-up in a patient with history of hepatitis C and steatohepatitis.

7 DRUG INTERACTIONS

Prior to ROCTAVIAN administration, the patient's existing medications should be reviewed to determine if they should be modified to prevent anticipated interactions described in this section.

Concomitant medications should be monitored after ROCTAVIAN administration, and the need to change concomitant medications based on patient's hepatic status and risk should be evaluated. When a new medication is started, close monitoring of ALT and factor VIII activity levels (e.g., weekly to every 2 weeks for the first month) is recommended to assess potential effects on both levels.

No in vivo interaction studies have been performed.

7.1 Isotretinoin

In one patient, decreased factor VIII activity without ALT elevation was detected after starting treatment with systemic isotretinoin following ROCTAVIAN infusion. Factor VIII activity was 75 IU/dL at Week 60 and transiently decreased to < 3 IU/dL at Week 64, after initiating isotretinoin. After discontinuing isotretinoin at Week 72, factor VIII activity recovered to 46 IU/dL at Week 122. An in vitro study in human primary hepatocytes indicated that isotretinoin suppressed factor VIII transcription independent of hepatotoxicity, without impact on ALT, and expression was partially restored upon cessation of isotretinoin treatment. Isotretinoin is not recommended in patients who are benefiting from ROCTAVIAN.

7.2 Efavirenz

One HIV positive patient treated with ROCTAVIAN at a dose of 4 × 10^13 vg/kg ROCTAVIAN while on an antiretroviral therapy regimen consisting of efavirenz, lamivudine, and tenofovir experienced asymptomatic elevations of ALT, AST, and GGT (> 5.0 × ULN) and serum bilirubin (> ULN and up to 1.5 × ULN) at Week 4 [see Use in Specific Populations (8.6)]. The reaction resolved after the antiretroviral therapy regimen was changed to a regimen without efavirenz. The patient later reverted to prophylactic use of factor VIII concentrates. An in vitro study in human primary hepatocytes indicated that efavirenz suppressed factor VIII transcription independent of hepatotoxicity, and expression was not restored upon discontinuation of efavirenz. Efavirenz is not recommended in patients treated with ROCTAVIAN.

7.3 Interactions with Agents that May Reduce or Increase Plasma Concentrations of Corticosteroids

Agents that may reduce or increase the plasma concentration of corticosteroids (e.g., agents that induce or inhibit cytochrome P450 3A4) can decrease the efficacy of the corticosteroid regimen or increase their side effects [see Dosage and Administration (2.3)].

7.4 Vaccinations

Prior to ROCTAVIAN infusion, ensure up to date vaccinations. Individual vaccination schedules may need to be adjusted to accommodate concomitant immunosuppressive therapy [see Dosage and Administration (2.3)]. Live vaccines should not be administered to patients while on immunosuppressive therapy.

8 USE IN SPECIFIC POPULATIONS

8.1 Pregnancy

Risk Summary

ROCTAVIAN is not intended for administration in women. There are no data on the use of ROCTAVIAN in pregnant women to inform a drug-associated risk of adverse developmental outcome. Animal reproduction and developmental toxicity studies have not been conducted with ROCTAVIAN. It is not known whether ROCTAVIAN can cause fetal harm when administered to a pregnant woman or can affect reproduction capacity.

The estimated background risk of major birth defects and miscarriage for the indicated population is unknown. In the US general population, the estimated background risk of major birth defects occurs in 2 to 4% of the general population and miscarriage occurs in 15 to 20% of clinically recognized pregnancies.

8.2 Lactation

Risk Summary

ROCTAVIAN is not intended for administration in women. There is no information regarding the presence of ROCTAVIAN in human milk, the effects on the breastfed infant, or the effects on milk production.

8.3 Females and Males of Reproductive Potential

ROCTAVIAN is not intended for administration in women.

Contraception After Administration to Males

In clinical studies, after administration of ROCTAVIAN, transgene DNA was detectable in semen [see Clinical Pharmacology (12.3)]. In nonclinical studies in healthy mice, the vector DNA was detected in the testes for at least 182 days post-administration of ROCTAVIAN at a dose level of 2.1 × 10^14 vg/kg [see Clinical Pharmacology (12.3)]. In a mating study in immune-deficient mice, ROCTAVIAN was not detected in liver tissues of offspring of naïve females mated with dosed males [see Nonclinical Toxicology (13.1)].

For 6 months after administration of ROCTAVIAN

- men of reproductive potential and their female partners must prevent or postpone pregnancy using an effective form of contraception, and
- men must not donate semen.

8.4 Pediatric Use

The safety and effectiveness of ROCTAVIAN in pediatric patients have not been established.

8.5 Geriatric Use

A single patient ≥ 65 years of age was treated with ROCATVIAN in clinical studies. Clinical studies of ROCTAVIAN did not include sufficient numbers of patients aged 65 and over to determine whether the efficacy or safety differs compared to younger patients.

8.6 Human Immunodeficiency Virus (HIV) Positive Patients

In clinical studies, 3 HIV infected patients have been treated with ROCTAVIAN. Clinical studies of ROCTAVIAN did not include sufficient numbers of patients with HIV to determine whether the efficacy and safety differs compared to patients without HIV infection.

A single HIV infected patient treated with ROCTAVIAN developed hepatocellular injury that subsequently resolved and was attributed to concomitant administration with antiretroviral drug efavirenz [see Drug Interactions (7.2)].

8.7 Factor VIII Inhibitors

The safety and effectiveness of ROCTAVIAN in patients with prior or active factor VIII inhibitors have not been established [see Clinical Pharmacology (12.6)]. Patients with active factor VIII inhibitors should not take ROCTAVIAN.

After administration of ROCTAVIAN, patients should be monitored for the development of factor VIII inhibitors by appropriate clinical observations and laboratory tests [see Warnings and Precautions (5.4)].

8.8 Hepatic Impairment

The safety and effectiveness of ROCTAVIAN in patients with hepatic impairment has not been established. Clinical studies excluded patients with known hepatic cirrhosis, significant fibrosis (stage 3 or 4 on the Batts-Ludwig scale or equivalent), current hepatitis B or C, or history of hepatic malignancy. No dose adjustments can be recommended for patients with hepatic impairment.

8.9 Renal Impairment

The safety and effectiveness of ROCTAVIAN in patients with renal impairment has not been established. No dose adjustments can be recommended for patients with renal impairment.

11 DESCRIPTION

ROCTAVIAN (valoctocogene roxaparvovec-rvox) is an adeno-associated virus (AAV) vector-based gene therapy product. ROCTAVIAN is replication-incompetent and consists of an AAV serotype 5 capsid containing a DNA sequence encoding the B-domain deleted SQ form of the human coagulation factor VIII (hFVIII-SQ). ROCTAVIAN is derived from naturally occurring adeno-associated virus and is produced using Sf9 insect cells and recombinant baculovirus technology.

ROCTAVIAN is a sterile suspension for intravenous infusion. When thawed, the suspension is clear and colorless to pale yellow.

Each vial of ROCTAVIAN contains an extractable volume of 8 mL of valoctocogene roxaparvovec-rvox at a concentration of 2 × 10^13 vector genomes (vg) per mL, and the following excipients: mannitol (20 mg/mL), poloxamer 188 (2.0 mg/mL), sodium chloride (8.2 mg/mL), sodium phosphate monobasic dihydrate (0.23 mg/mL), sodium phosphate dibasic dodecahydrate (3.05 mg/mL) and Water for Injection, USP. The pH of ROCTAVIAN is 6.9 to 7.8. The osmolarity of ROCTAVIAN is 364 to 445 mOsm/L.

The product contains no preservative.

12 CLINICAL PHARMACOLOGY

12.1 Mechanism of Action

Valoctocogene roxaparvovec-rvox is an adeno-associated virus serotype 5 (AAV5) based gene therapy vector, designed to introduce a functional copy of a transgene encoding the B-domain deleted SQ form of human coagulation factor VIII (hFVIII-SQ). Transcription of this transgene occurs within the liver, using a liver-specific promoter, which results in the expression of hFVIII-SQ. The expressed hFVIII-SQ replaces the missing coagulation factor VIII needed for effective hemostasis.

12.2 Pharmacodynamics

Following ROCTAVIAN infusion, vector DNA is processed in vivo to form full-length, episomal transgenes that increase circulating hFVIII-SQ up to 5 years.

Liver samples from 5 patients in clinical studies collected 0.5-4.1 years post-dose were analyzed. Vector integration into human genomic DNA was observed in all samples. No preferential integration of the vector and no clonal outgrowth of cells as a result of vector integration was observed. ROCTAVIAN can also insert into DNA of other human body cells; vector insertion into parotid gland DNA samples without associated clinical manifestations was observed in one patient treated with ROCTAVIAN.

Factor VIII Activity

The pharmacodynamic effect of ROCTAVIAN was assessed by measuring circulating factor VIII activity levels.

Factor VIII activity levels (IU/dL) over time post-ROCTAVIAN infusion in ITT population are reported by both the CSA and OSA. The mean factor VIII activity levels at Month 36 was 18.2 IU/dL (95% CI: 12.9, 23.4) using the CSA, a statistically significant (p < 0.0001) improvement from 1 IU/dL at baseline.

Table 7 shows factor VIII activity levels (IU/dL) over time post-ROCTAVIAN infusion in patients rolled over from a non-interventional study prospectively collecting patients' baseline annualized bleeding rate (ABR) and factor VIII usage data.

Table 7: Factor VIII Activity Levels (IU/dL) Over Time
Timepoint | Rollover Population N = 112 |  | Directly Enrolled Population N = 22
 | CSA | OSA | CSA | OSA
Month 3 | N = 111 | N = 111 | N = 22 | N = 22
Mean (SD) | 34.9 (40.4) | 54.6 (60.8) | 31.4 (25.7) | 48.3 (36.0)
Median (Q1, Q3) | 20.7 (10.3, 40.5) | 31.3 (15.3, 71.7) | 20.9 (12.6, 45.7) | 36.0 (22.4, 63.9)
Min, Max | 0, 249.5 | 1.5, 335.8 | 0, 85.8 | 4.5, 126.0
Month 6 | N = 111 | N = 111 | N = 22 | N = 22
Mean (SD) | 55.4 (57.5) | 84.9 (83.1) | 40.0 (37.9) | 63.0 (57.2)
Median (Q1, Q3) | 38.8 (16.8, 76.5) | 62.0 (28.0, 115.2) | 33.2 (14.7, 46.3) | 53.5 (23.7, 78.2)
Min, Max | 0, 367.3 | 1.9, 483.9 | 0, 169.4 | 1.8, 261.9
Month 10 | N = 111 | N = 111 | N = 20 | N = 20
Mean (SD) | 49.4 (49.5) | 73.6 (70.5) | 44.2 (49.6) | 70.2 (70.9)
Median (Q1, Q3) | 31.7 (17.1, 64.5) | 51.3 (25.1, 96.2) | 30.9 (14.1, 68.6) | 55.4 (24.8, 101.4)
Min, Max | 0, 265.3 | 1.2, 375.6 | 0, 223.6 | 2.4, 313.7
Month 12 | N = 111 | N = 111 | N = 21 | N = 21
Mean (SD) | 43.6 (45.5) | 64.7 (64.6) | 38.2 (46.3) | 59.7 (67.0)
Median (Q1, Q3) | 24.0 (12.5, 63.7) | 40.0 (20.4, 87.5) | 23.9 (11.2, 52.8) | 40.5 (17.4, 82.6)
Min, Max | 0, 231.2 | 0, 311.1 | 1.6, 207.4 | 4.4, 294.1
Month 18 | N = 99 | N = 99 | N = 18 | N = 18
Mean (SD) | 27.7 (32.3) | 40.6 (45.9) | 28.5 (28.9) | 44.5 (43.9)
Median (Q1, Q3) | 13.5 (6.9, 36.8) | 22.5 (10.9, 55.30) | 15.3 (10.8, 43.9) | 24.4 (17.7, 60.4)
Min, Max | 0, 167.9 | 0, 232.2 | 3.3, 117.0 | 4.2, 173.7
Month 24 | N = 98 | N = 99 | N = 19 | N = 18
Mean (SD) | 25.0 (35.5) | 38.9 (50.7) | 22.0 (28.7) | 36.0 (40.8)
Median (Q1, Q3) | 12.7 (5.1, 26.5) | 22.7 (7.9, 45.7) | 8.9 (5.8, 25.9) | 19.5 (7.9, 37.7)
Min, Max | 0, 187.1 | 0, 271.3 | 0, 110.6 | 2.4, 146.7
Month 36 | N = 96 | N = 97 | N = 15 | N = 15
Mean (SD) | 21.0 (34.0) | 33.8 (47.6) | 20.8 (24.4) | 32.2 (33.1)
Median (Q1, Q3) | 10.0 (4.3, 19.8) | 17.7 (7.2, 35.1) | 9.4 (6.6, 31.7) | 20.6 (8.5, 46.7)
Min, Max | 0, 217.7 | 0, 291.4 | 0, 74.5 | 1.9, 104.2

The proportion of patients achieving factor VIII activity level thresholds by year are presented in Table 8 by both the CSA and OSA. The majority (95%) of patients who reach factor VIII activity levels of ≥ 5 IU/dL using the CSA do so within 5 months post-infusion.

Table 8: Patients Achieving Factor VIII Activity Thresholds by Year
Rollover Population (N = 112)
Factor VIII Activity Threshold Achieved by Assay | Year 1 N = 111 n (%) | Year 2 N = 98 n (%) | Year 3 N = 96 n (%)
CSA
> 150 IU/dL | 6 (5%) | 2 (2%) | 2 (2%)
40 - ≤ 150 IU/dL | 37 (33%) | 14 (14%) | 9 (9%)
15 - < 40 IU/dL | 37 (33%) | 27 (28%) | 23 (24%)
5 - < 15 IU/dL | 18 (16%) | 33 (34%) | 35 (36%)
3 - < 5 IU/dL | 3 (3%) | 10 (10%) | 8 (8%)
< 3 IU/dL | 10 (9%) | 12 (12%) | 19 (20%)
 | Year 1 N = 111 n (%) | Year 2 N = 99 n (%) | Year 3 N = 97 n (%)
OSA
> 150 IU/dL | 12 (11%) | 5 (5%) | 4 (4%)
40 - ≤ 150 IU/dL | 44 (40%) | 25 (25%) | 17 (18%)
15 - < 40 IU/dL | 37 (33%) | 36 (36%) | 36 (37%)
5 - < 15 IU/dL | 10 (9%) | 20 (20%) | 26 (27%)
1 - < 5 IU/dL | 6 (5%) | 11 (11%) | 12 (12%)
< 1 IU/dL | 2 (2%) | 2 (2%) | 2 (2%)
Directly Enrolled Population (N = 22)
Factor VIII Activity Threshold Achieved by Assay | Year 1 N = 21 n (%) | Year 2 N = 19 n (%) | Year 3 N = 15 n (%)
CSA
> 150 IU/dL | 1 (5%) | 0 (0%) | 0 (0%)
40 - ≤ 150 IU/dL | 5 (24%) | 3 (16%) | 3 (20%)
15 - < 40 IU/dL | 8 (38%) | 4 (21%) | 2 (13%)
5 - < 15 IU/dL | 5 (24%) | 8 (42%) | 7 (47%)
3 - < 5 IU/dL | 0 (0%) | 1 (5%) | 1 (7%)
< 3 IU/dL | 2 (10%) | 3 (16%) | 2 (13%)
 | Year 1 N = 21 n (%) | Year 2 N = 18 n (%) | Year 3 N = 15 n (%)
OSA
> 150 IU/dL | 1 (5%) | 0 (0%) | 0 (0%)
40 - ≤ 150 IU/dL | 10 (48%) | 4 (22%) | 4 (27%)
15 - < 40 IU/dL | 6 (29%) | 6 (33%) | 6 (40%)
5 - < 15 IU/dL | 3 (14%) | 6 (33%) | 3 (20%)
1 - < 5 IU/dL | 1 (5%) | 2 (11%) | 2 (13%)
< 1 IU/dL | 0 (0%) | 0 (0%) | 0 (0%)

Specific Populations

A trend of lower factor VIII activity levels was observed in Black patients within the study population. The mean (SD) peak factor VIII activity levels measured by chromogenic assay were 37.2 (27.5) IU/dL and 90.8 (84.5) IU/dL for Black patients and patients of other races (Asian, White and others). Given the small sample size, the limited number of sites enrolling Black patients relative to the total population, the existence of potential confounding factors, and multiple posthoc analyses, this trend was insufficient to allow meaningful conclusions about the differences in response rates based on race or other factors therein influencing factor VIII expression following ROCTAVIAN infusion. Despite differences in factor VIII activity levels, ABR and annualized factor VIII usage was similar across races.

12.3 Pharmacokinetics

Biodistribution (within the body) and Vector Shedding (excretion/secretion)

Valoctocogene roxaparvovec-rvox transgene DNA levels (total amount of vector DNA) in various tissues (evaluated in nonclinical studies), blood, and shedding matrices were determined using a quantitative polymerase chain reaction (qPCR) assay. This assay is sensitive to transgene DNA, including fragments of degraded DNA. It does not indicate whether DNA is present in the vector capsid, in cells or in the fluid phase of the matrix (e.g., blood plasma, seminal fluid), or whether intact vector is present. Plasma and semen matrices were further evaluated by measuring encapsidated (potentially infectious) vector DNA using an immunoprecipitation quantitative PCR assay in Studies 270-201 and 270-301.

Nonclinical Data

Biodistribution of ROCTAVIAN was assessed in adult male mice. Following intravenous administration of 2.1 × 10^14 vg/kg, the highest vector DNA concentration was detected in the liver, followed by lower levels in the lung, heart, lymph nodes, kidney, spleen, bone marrow, testis, and brain through six months post-administration. The expression of the hFVIII mRNA transcripts were primarily detected in the liver, with no or minimal expression in extrahepatic tissues.

Clinical Data

ROCTAVIAN biodistribution and vector shedding were investigated on samples from blood, saliva, semen, stool, and urine. Administration of ROCTAVIAN at the dose of 6 × 10^13 vg/kg resulted in detectable vector DNA in blood and all shedding matrices evaluated at the dose of 6 × 10^13 vg/kg, with peak concentrations observed between 1 and 9 days post-administration. The peak vector DNA concentrations were observed in blood, followed by saliva, semen, stool, and urine. The peak concentration observed to date in blood across two clinical studies was 2 × 10^11 vg/mL. The maximum concentration observed in any shedding matrix was 1 × 10^10 vg/mL. After reaching the maximum in a matrix, the transgene DNA concentration declines steadily.

In patients treated in two clinical studies, encapsidated (potentially transmissible) vector DNA was detectable in plasma up to 10 weeks after ROCTAVIAN administration.

All patients treated in clinical studies achieved the first of 3 consecutive measurements below the lower limit of quantification (LLOQ) for vector DNA in semen by 36 weeks, and all except one patient achieved 3 consecutive measurements below limit of detection (BLOD) or negative by the time of the data cut. The maximum time to the first of 3 consecutive measurements BLOD for encapsidated (potentially transmissible) vector DNA in semen was 12 weeks.

In clinical studies, all patients achieved 3 consecutive measurements below the LLOQ for vector DNA in urine and saliva, and 126 (89%) patients achieved 3 consecutive measurements below the LLOQ for vector DNA in stool by the time of the data cut. The maximum time to the first of 3 consecutive LLOQ measurements was 8 weeks for urine, 52 weeks for saliva, and 131 weeks for stool. All patients in the first study achieved 3 consecutive measurements BLOD or negative in urine, saliva, and stool by five-year post-dosing. All patients in the second study achieved 3 consecutive measurements BLOD or negative in urine, and saliva, and 85 (63%) patients achieved 3 consecutive measurements BLOD or negative in stool by three-year data cut.

Magnitude and duration of shedding appear to be independent of the patient's attained factor VIII activity.

12.6 Immunogenicity

The observed incidence of anti-drug antibodies is highly dependent on the sensitivity and specificity of the assay. Differences in assay methods preclude meaningful comparisons of the incidence of anti-drug antibodies in the studies described below with the incidence of anti-drug antibodies in other studies, including those of ROCTAVIAN or of other adeno-associated virus-based gene therapy products.

In clinical studies, all patients receiving treatment were required to screen negative for anti-AAV5 antibodies and negative (< 0.6 BU) for factor VIII inhibitors in a Nijmegen modified Bethesda assay following a lifetime minimum of 150 exposure days to factor VIII replacement therapy [see Use in Specific Populations (8.7)]. Following infusion of ROCTAVIAN, all patients remained negative for factor VIII inhibitors.

All patients seroconverted to anti-AAV5 antibody positive within 8 weeks of administration. Anti-AAV5 total antibody titers peaked by 36 weeks after administration with mean (SD) values of 12,528,983 (32,427,817), and remained stable until the last time point tested, Week 168 with mean (SD) values of 3,673,038 (3,344,713).

ROCTAVIAN-treated patients were tested for cellular immune responses against the AAV5 capsid and the factor VIII transgene product using an IFN-γ ELISpot assay. AAV5 capsid-specific cellular immune responses were detected beginning at Week 2 following dose administration and often declined or reverted to negative over the first 52 weeks in the majority of patients with available data. Incidence peaked at Week 2 with 67 of 96 patients (70%) testing positive in the IFN-γ ELISpot assay. This declined to 17 of 74 patients (23%) at Week 26, and 10 of 60 patients (17%) at Week 52.

Factor VIII-specific cellular responses were detected in 81 of 123 (65.9%) patients, often sporadically at a single time point and reverting to negative in most patients.

13 NONCLINICAL TOXICOLOGY

13.1 Carcinogenesis, Mutagenesis, Impairment of Fertility

No animal studies have been conducted to evaluate the effects of ROCTAVIAN on carcinogenesis.

To evaluate vector integration, host genomic DNA was isolated from liver tissues obtained from nonhuman primates at 13 and 26 weeks following intravenous administration of ROCTAVIAN at dose levels of up to 5.4 × 10^13 vg/kg. Vector DNA was mostly detected in the form of episomal DNA that was not integrated into the host genome. Vector integration events were observed at low frequencies and distributed throughout the host genome with no indication of clonal enrichment or preference to particular chromosomal locations, including genes associated with oncogenesis in humans [see Warnings and Precautions (5.5) and Clinical Pharmacology (12.2)].

Since ROCTAVIAN vector DNA was detected in testes of adult male mice for at least 6 months following a single intravenous administration at dose level of 2.1 × 10^14 vg/kg [see Clinical Pharmacology (12.3)], the potential for vertical transmission to offspring was studied in Rag2-/- immunodeficient mice. A single intravenous administration of ROCTAVIAN at a dose level of 6.7 × 10^13 vg/kg into male immunodeficient mice that were mated 37 days later with naïve female mice did not result in adverse effects on fertility rates, pregnancy rates, and litter sizes. Quantitative polymerase chain reaction (qPCR) evaluation of liver tissues from the F1 pups did not detect the vector DNA.

13.2 Animal Toxicology and/or Pharmacology

A single intravenous administration of up to 2.1 × 10^14 vg/kg of ROCTAVIAN in immunocompetent male mice with intact coagulation (CD1 mice), followed by an observation period of up to 26 weeks, showed dose-dependent toxicities in the heart, lung, thymus, and epididymis. At dose levels of 6.5 × 10^13 vg/kg and higher, histopathologic findings in the heart included minimal to moderate epicardial hemorrhage, myocardial necrosis, fibrosis, inflammation, and vascular/perivascular necrosis, minimal to mild mesothelial hypertrophy/hyperplasia, fibroplasia, myocardial atrophy, and vascular/perivascular mixed cell infiltrates. Lung findings included moderate to marked hemorrhage, minimal to mild edema, vascular/perivascular necrosis, and mesothelial hypertrophy. Additional ROCTAVIAN-related findings included mild fibrosis, hemorrhage, and pigmented macrophages in the epididymis, and moderate to marked hemorrhage and hypocellularity of the thymus. ROCTAVIAN-related mortality, adverse clinical observations, and changes in gross pathology were observed at dose levels of 6.5 × 10^13 vg/kg and higher, and were associated with fibrosis, hemorrhage, and necrosis in the heart.

In a toxicology study conducted in adult male nonhuman primates with a duration of 3 months, single intravenous administration of ROCTAVIAN at dose levels of 1.6 × 10^13 vg/kg and 5.4 × 10^13 vg/kg resulted in a dose-dependent prolongation of activated partial thromboplastin time (APTT). The transient APTT prolongation in a subset of nonhuman primates was temporally associated with an immune response to hFVIII-SQ protein. At 3 months post-administration, histopathology findings included minimal to mild mononuclear/mixed infiltration in the lungs.

14 CLINICAL STUDIES

The efficacy of ROCTAVIAN was evaluated in a prospective, phase 3, open-label, single-dose, single-arm, multinational study in 134 adult males (18 years of age and older) with severe hemophilia A, who received a single intravenous dose of 6 × 10^13 vg/kg body weight of ROCTAVIAN and entered a follow-up period of 5 years. Patients previously treated with prophylactic factor VIII replacement therapy, but not emicizumab, were enrolled in the study. The study population was 72% White, 14% Asian, and 11% Black with a median age of 30 (range: 18 to 70) years. Twenty patients had a history of hepatitis B and 41 patients had a history of hepatitis C. All except 2 patients were HIV-negative.

Only patients without detectable, pre-existing antibodies to AAV5 capsid were eligible for therapy. Presence of pre-existing antibodies to AAV5 capsid was identified during screening using the ARUP Laboratories AAV5 DetectCDx™ total antibody assay, which is the FDA-approved test for selection of patients for ROCTAVIAN therapy. Other key exclusion criteria included active infection, chronic or active hepatitis B or C, immunosuppressive disorder including HIV, current or prior history of factor VIII inhibitor, stage 3 or 4 liver fibrosis, cirrhosis, liver function test abnormalities, history of thrombosis or thrombophilia, serum creatinine ≥ 1.4 mg/dL, and active malignancy.

Of the 134 patients who received ROCTAVIAN in the clinical trial, 112 patients had baseline annualized bleeding rate (ABR) data prospectively collected during a period of at least six months on factor VIII prophylaxis prior to receiving ROCTAVIAN (rollover population). The remaining 22 patients had baseline ABR collected retrospectively (directly enrolled population). All patients were followed for at least 3 years.

The primary efficacy outcome was a non-inferiority (NI) test of the difference in ABR in the efficacy evaluation period (EEP) following ROCTAVIAN administration compared with ABR during the baseline period in the rollover population. The NI margin was 3.5 bleeds per year. All bleeding episodes, regardless of treatment, were counted towards ABR. The EEP started from Study Day 33 (Week 5) or the end of factor VIII prophylaxis including a washout period after ROCTAVIAN treatment, whichever was later, and ended when a patient completed the study, had the last visit, or withdrew or was lost to follow-up from the study, whichever was the earliest.

Table 9 summarizes the NI comparison between the mean ABR after ROCTAVIAN treatment and the mean baseline ABR while patients were on factor VIII prophylaxis in the rollover population (N = 112). The mean EEP ABR was 2.6 bleeds/year, compared to a mean baseline ABR of 5.4 bleeds/year. The mean difference in ABR was -2.8 (95% confidence interval: -4.3, -1.2) bleeds/year. The NI analysis met the pre-specified NI margin, indicating the effectiveness of ROCTAVIAN.

A majority of patients treated with ROCTAVIAN received immunosuppressive medications, including steroids, to control elevations in transaminases and to prevent loss of transgene expression [see Dosage and Administration (2.3), Warnings and Precautions (5.2), and Adverse Reactions (6.1)].

Table 9: Summary of ABRs and Bleeding Events (Rollover Population, N = 112)
ABR and Bleeding Events | Baseline | Post-ROCTAVIAN Efficacy Evaluation Period
Median (range) follow-up duration in years | 0.6 (0.5, 1.3) | 3.0 (1.7, 3.7)
Follow-up duration in person-years | 78.3 | 342.8
Mean (SD) ABR in bleeds/year | 5.4 (6.9) | 2.6 (6.2) [A total of 13 patients (12%) had used factor VIII replacement products or emicizumab during the efficacy evaluation period for prophylaxis, with a median start time at 2.3 (range: 0.1 to 3.3) years. An ABR of 35 was imputed for the periods when these patients were on prophylaxis.]
Median (min, max) ABR in bleeds/year | 3.3 (0, 34.6) | 0.3 (0, 35.0)
Observed spontaneous bleed count (proportion of total bleeds) | 176 (42%) | 179 (41%)
Observed joint bleed count (proportion of total bleeds) | 240 (57%) | 195 (45%)
Min: Minimum; Max: Maximum; SD: Standard Deviation

In the rollover population, a total of 5 patients (4%) did not respond and 17 patients (15%) lost response to ROCTAVIAN treatment over a median time of 2.3 (range: 1.0 to 3.3) years. In the directly enrolled population with a longer follow-up, a total of 1 patient (5%) did not respond and 6 patients (27%) lost response to ROCTAVIAN treatment over a median time of 3.6 (range: 1.2 to 4.3) years.

16 HOW SUPPLIED/STORAGE AND HANDLING

16.1 How Supplied

ROCTAVIAN (valoctocogene roxaparvovec-rvox) injection is supplied as a sterile, preservative-free, clear and colorless to pale yellow suspension for intravenous infusion. ROCTAVIAN contains 2 × 10^13 vector genomes (vg) per mL.

Each carton of ROCTAVIAN (NDC 68135-927-48) contains one single-dose vial (NDC 68135-927-01) with an extractable volume of not less than 8 mL, containing 16 × 10^13 vector genomes (vg).

16.2 Storage and Handling

Product as Packaged for Sale

Transport frozen at ≤ -60°C (-76°F)

Store upright at ≤ -60°C (-76°F).

Store ROCTAVIAN vial in carton until ready to use.

Protect ROCTAVIAN from light.

During Preparation and Administration

Thaw at room temperature, up to 25°C (77°F).

After thawing, ROCTAVIAN can be held at room temperature for a maximum of 10 hours, including preparation and infusion times [see Dosage and Administration (2.2)].

If necessary, an intact vial (stopper not yet punctured) that has been thawed can be stored refrigerated (2 to 8 °C) for up to 3 days, upright and protected from light (e.g., in the original carton).

Do not expose ROCTAVIAN to the light of an ultraviolet radiation disinfection lamp.

Once thawed, DO NOT REFREEZE.

Treat spills of ROCTAVIAN with a virucidal agent with proven activity against non-enveloped viruses and blot using absorbent materials.

Dispose of unused product and disposable materials that may have come in contact with ROCTAVIAN in accordance with local guidance for pharmaceutical waste.

17 PATIENT COUNSELING INFORMATION

Inform patients of the following risks and required precautions prior to ROCTAVIAN infusion:

Pre-Infusion Assessments

Inform patients that prior to dosing ROCTAVIAN the following will be necessary:

- Blood tests to look for factor VIII inhibitors and detect antibodies to AAV5. If these tests are positive, the patient will not be a candidate for ROCTAVIAN [see Dosage and Administration (2) and Use in Special Populations (12.6)].
- Liver health assessments, which include measuring liver function tests, liver ultrasound, and elastography or laboratory assessments for assessing hepatic fibrosis. If these tests are abnormal, the patient may not be a good candidate for ROCTAVIAN [see Dosage and Administration (2)].
- Assessment for suitability for corticosteroids and/or other immunosuppressive therapy. Inform patients that they may receive corticosteroids and/or other immunosuppressive agents for an extended period of time and communicate any risks associated with these therapies. The baseline assessment for suitability for immunosuppression may deem that the patient is not a good candidate for immunosuppression and hence not a good candidate for ROCTAVIAN [see Dosage and Administration (2, 2.3)].

Adverse Reactions During and After Infusion

- Inform patients that infusion reactions including anaphylaxis have occurred. Patients will be monitored during and for at least 3 hours after infusion [see Warnings and Precautions (5.1)].
- Educate patients on possible symptoms of infusion reactions during and after infusion and advise them to immediately inform medical staff if they experience such a reaction [see Dosage and Administration (2.3) and Warnings and Precautions (5.1)]. When discharging the patient, provide instructions on actions in case of a new or recurrent reaction and when to seek medical attention.

Importance of Liver Enzyme and Factor VIII Level Monitoring

- ROCTAVIAN can cause elevation of certain liver enzymes. Elevation in liver enzymes may be associated with decrease in factor VIII activity [see Warnings and Precautions (5.2)].
- Weekly blood test will be required for at least 26 weeks for monitoring this. Monitoring beyond this time is usually less frequent but depends on clinical situation, prior laboratory test results, and ongoing treatment with corticosteroids or other immunosuppressive therapy. [see Dosage and Administration (2.3)].

Use of Factor VIII Concentrates/Hemostatic Agents after Treatment with ROCTAVIAN

- Advise patients on tapering factor VIII concentrates/hemostatic agents and, as necessary, on whether and how to continue or re-start their use, and on actions in case of invasive procedures, surgery, trauma, or bleeds [see Dosage and Administration (2.3)].
- Advise patients that not all patients may respond to ROCTAVIAN and that currently it is not possible to predict who will respond and how long the treatment response will continue. Counsel patients, as necessary, on when they may need to re-instate prophylactic use of factor VIII concentrates/hemostatic agents [see Dosage and Administration (2.3)].

Corticosteroid Regimen and Alternate Immunosuppression

- Inform patients undergoing corticosteroid treatment to adhere to the regimen and about potential adverse reactions and necessary precautions [see Dosage and Administration (2.3) and Warnings and Precautions (5.2)].
- Advise patients that treatment with immunosuppressive agents other than corticosteroids may be required in case of intolerance, or adverse event from or failure of corticosteroid therapy [see Dosage and Administration (2.3)].

Hepatic Health

- Advise patients on how to maintain or improve hepatic health. Advise patients that they should abstain from consuming alcohol for at least one year after treatment and how much alcohol may be acceptable for them in the longer term [see Warnings and Precautions (5.2)].
- Advise patients not to use any medications, herbal products, or supplements without first confirming with a health professional that they are not hepatotoxic. Instruct patients that they or their healthcare professional contact you if use of a hepatotoxic agent appears unavoidable, to discuss potential alternatives and any implications for patient monitoring i.e., more frequent monitoring of liver enzymes and factor VIII activity may be needed [see Warnings and Precautions (5.2) and Drug Interactions (7)].

Thromboembolic Events

- Inform patients that elevated factor VIII activity above the upper limit of normal has occurred following ROCTAVIAN administration. Elevated factor VIII activity above the upper limit of normal may increase the risk of a thromboembolic event [see Warnings and Precautions (5.3)].
- As necessary, advise patients of their risk factors for thrombotic events and general cardiovascular risk factors, how to minimize their risk, how to recognize a thrombotic event and to seek immediate medical attention if they observe signs or symptoms that can indicate a thrombotic event [see Warnings and Precautions (5.3)].

Contraception and Semen Donation

- Advise patients that, after a male patient has been treated with ROCTAVIAN, the patient and/or his female partner must avoid pregnancy for a period of 6 months, and that male patients must not donate semen for a period of 6 months [see Use in Specific Populations (8.3)].
- Instruct patients on acceptable methods of contraception.

Blood, Organ, Tissue and Cell Donation

- Advise patients not to donate blood, organs, tissues, and cells for transplantation after treatment with ROCTAVIAN.

Repeat Treatment and Impact on Receiving Other AAV Gene Therapies

- Advise patients that ROCTAVIAN is a one-time treatment. Currently, treatment with ROCTAVIAN precludes the patient from receiving another gene therapy for hemophilia.

Malignancy

- Inform patients that since ROCTAVIAN is a liver-directed AAV therapy, there may be a theoretical risk of hepatocellular carcinoma. Patients with risk factors for hepatocellular carcinoma should be monitored regularly for 5 years with regular ultrasound and blood tests (alpha-fetoprotein). No malignancies assessed as being likely related to ROCTAVIAN treatment have been reported in clinical trials. Since the vector can insert into DNA of any cell, other malignancies may also occur [see Warnings and Precautions (5.5)].
- Advise patients to contact BioMarin Pharmaceutical Inc. (1-866-906-6100) if they are diagnosed with any malignancy [see Warnings and Precautions (5.5)].

Long-Term Follow-Up

- Inform patients that they should be enrolled in a 15-year registry to evaluate the long-term efficacy and safety of hemophilia treatments.

Manufactured by:
BioMarin Pharmaceutical Inc.
Novato, CA 94949
US License Number 1649

PRINCIPAL DISPLAY PANEL - 8 mL Vial Label

NDC 68135-927-01
Rx only

valoctocogene roxaparvovec-rvox

ROCTAVIAN™

Suspension for intravenous infusion

16 x 10^13 vector genomes/8 mL
(2 x 10^13 vector genomes/mL)

BioMarin Pharmaceutical Inc.
Novato, CA 94949
US License No. 1649

Single-dose

Discard unused portion

BiOMARIN®

PRINCIPAL DISPLAY PANEL - 8 mL Vial Carton

Rx only
NDC 68135-927-48

valoctocogene
roxaparvovec-rvox

ROCTAVIAN™

Suspension for intravenous infusion

16 x 10^13 vector genomes/8 mL
(2 x 10^13 vector genomes/mL)

Contains one single-dose vial.

BiOMARIN®